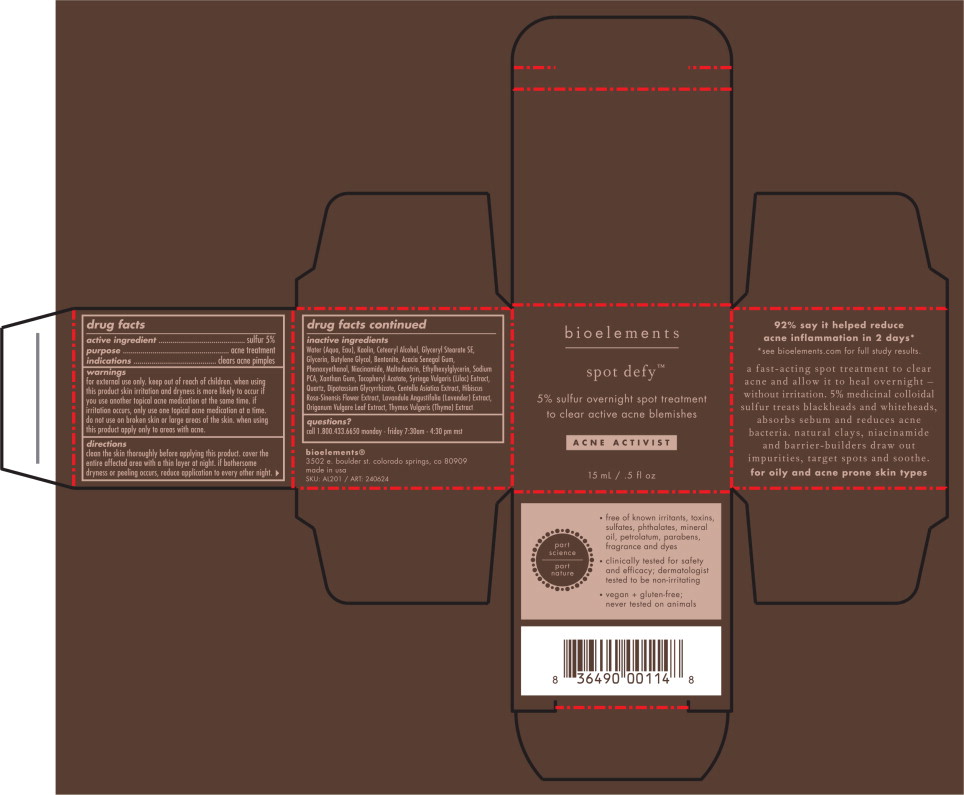 DRUG LABEL: Spot Defy
NDC: 49825-200 | Form: LOTION
Manufacturer: Bioelements, Inc.
Category: otc | Type: HUMAN OTC DRUG LABEL
Date: 20251217

ACTIVE INGREDIENTS: SULFUR 50 mg/1 mL
INACTIVE INGREDIENTS: WATER; KAOLIN; CETOSTEARYL ALCOHOL; GLYCERYL STEARATE SE; GLYCERIN; BUTYLENE GLYCOL; BENTONITE; ACACIA; PHENOXYETHANOL; NIACINAMIDE; MALTODEXTRIN; ETHYLHEXYLGLYCERIN; SODIUM PYRROLIDONE CARBOXYLATE; XANTHAN GUM; .ALPHA.-TOCOPHEROL ACETATE; SYRINGA VULGARIS FLOWER; GLYCYRRHIZINATE DIPOTASSIUM; CENTELLA ASIATICA WHOLE; HIBISCUS ROSA-SINENSIS FLOWER; LAVANDULA ANGUSTIFOLIA WHOLE; OREGANO; THYME

Spot Defy

active ingredient

sulfur 5%

purpose

acne treatment

indications

clears acne pimples

warnings

for external use only.

keep out of reach of children.

when using this product skin irritation and dryness is more likely to occur if you use another topical acne medication at the same time. if irritation occurs, only use one topical acne medication at a time.

do not use on broken skin or large areas of the skin.

when using this product apply only to areas with acne.

directions

clean the skin thoroughly before applying this product. cover the entire affected area with a thin layer at night. if bothersome dryness or peeling occurs, reduce application to every other night.

inactive ingredients

Water (Aqua, Eau), Kaolin, Cetearyl Alcohol, Glyceryl Stearate SE, Glycerin, Butylene Glycol, Bentonite, Acacia Senegal Gum, Phenoxyethanol, Niacinamide, Maltodextrin, Ethylhexylglycerin, Sodium PCA, Xanthan Gum, Tocopheryl Acetate, Syringa Vulgaris (Lilac) Extract, Quartz, Dipotossium Glycyrrhizate, Centella Asiatica Extract, Hibiscus Rosa-Sinensis Flower Extract, Lavandula Angustifolia (Lavender) Extract, Origanum Vulgare Leaf Extract, Thymus Vulgaris (Thyme) Extract

questions?

call 1.800.433.6650 monday - friday 7:30am - 4:30 pm mst

Principal Display Panel – 15 mL Carton Label

bioelements

spot defy™

5% sulfur overnight spot treatment
to clear active acne blemishes

ACNE ACTIVIST

15 mL / .5 fl oz